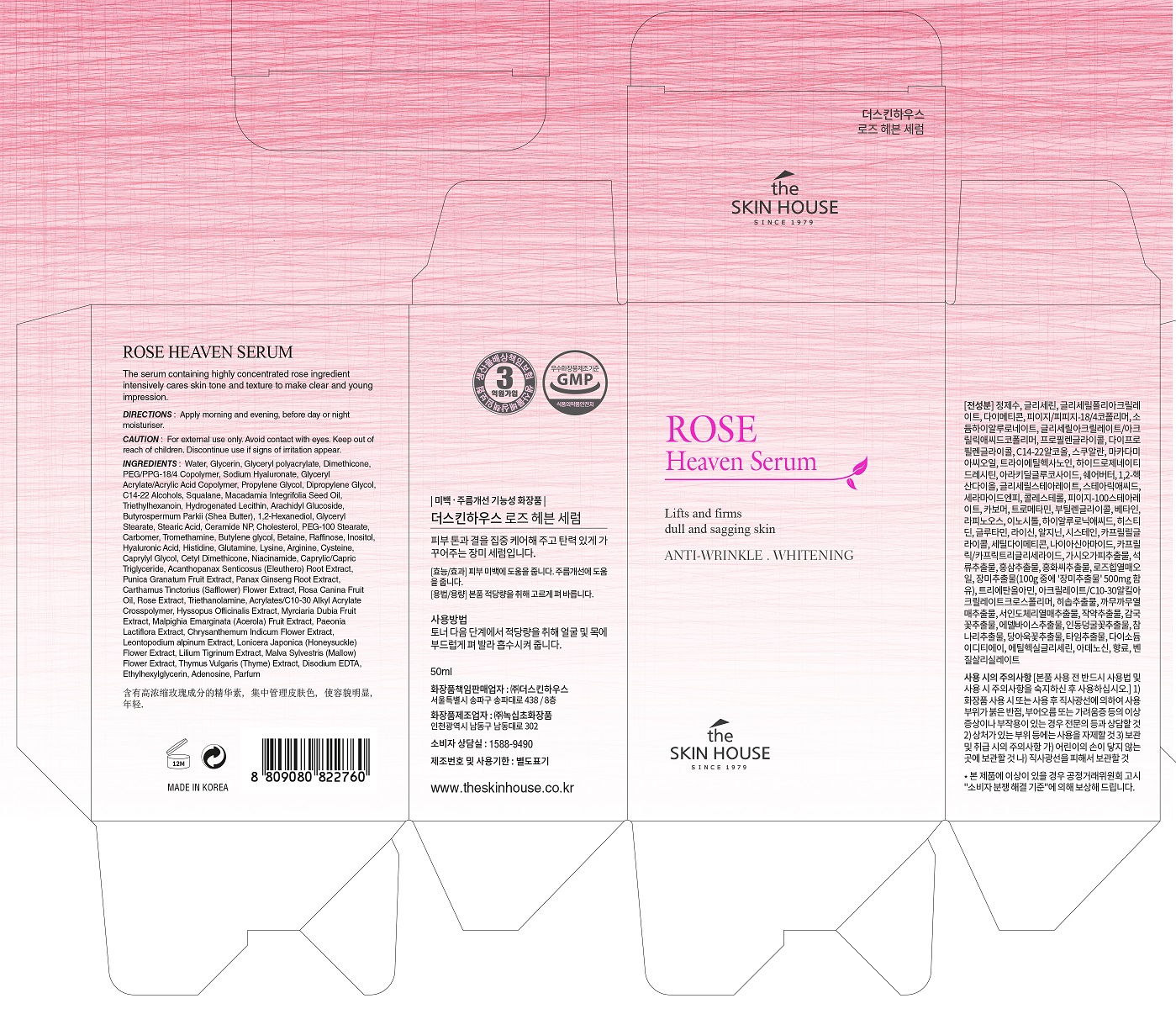 DRUG LABEL: THE SKIN HOUSE ROSE HEAVEN SERUM
NDC: 73590-0024 | Form: LIQUID
Manufacturer: NOKSIBCHO cosmetic Co., Ltd.
Category: otc | Type: HUMAN OTC DRUG LABEL
Date: 20200330

ACTIVE INGREDIENTS: NIACINAMIDE 2 g/100 mL; ADENOSINE 0.04 g/100 mL
INACTIVE INGREDIENTS: WATER

Drug Facts

ACTIVE INGREDIENT

Adenosine, Niacinamide

INACTIVE INGREDIENT

Water
Glycerin
Glyceryl polyacrylate
PEG/PPG-18/4 Copolymer
Sodium Hyaluronate
Phenoxy ethanol
Glyceryl Acrylate/Acrylic Acid Copolymer
Propylene Glycol
Dipropylene Glycol
Dimethicone
C14-22 Alcohols
Squalane
Macadamia Integrifolia Seed Oil
Triethylhexanoin
Hydrogenated Lecithin
Arachidyl Glucoside
Butyrospermum Parkii (Shea Butter)
Glyceryl Stearate
Stearic Acid
Ceramide NP
Cholesterol
PEG-100 Stearate
Carbomer
Tromethamine
Butylene glycol
Betaine
Raffinose
Inositol
Hyaluronic Acid
Histidine
Glutamine
Lysine
Arginine
Cysteine
Caprylyl Glycol
1,2-Hexanediol
Cetyl Dimethicone
1,3 Butylene glycol
Caprylic/Capric Triglyceride
Acanthopanax Senticosus (Eleuthero) Root Extract
Punica Granatum Fruit Extract
Panax Ginseng Root Extract
Carthamus Tinctorius (Safflower) Flower Extract
Rosa Canina Fruit Oil
Red ginseng Root Extract
Rose Extract
Triethanolamine
Acrylates/C10-30 Alkyl Acrylate Crosspolymer
Hyssopus Officinalis Extract
Myrciaria Dubia
Fruit Extract
Malpighia Emarginata
(Acerola) Fruit Extract
Paeonia Lactiflora Bark/Sap Extract
Chrysanthemum Indicum Flower Extract
Leontopodium alpinum extract
Lonicera Japonica (Honeysuckle) Flower Extract
Lilium Tigrinum Extract
Malva Sylvestris (Mallow) Flower Extract
Thymus Vulgaris (Thyme) Extract
Disodium EDTA
Ethylhexylglycerin
Parfum

PURPOSE

- Anti-aging & brightening toner

A U-shape clear essence toner enables the skin to become nutritious.

Rose extracts, rose hips oil and other 14 kinds of natural extracts make the dehydrated skin to become moist, bright, smooth and more vital. Skin can absorb the toner without leaving stickiness and the toner gives a energy to skin instantly. Also, the delicate rose-scented gives elegant and classy feelings.

It is a toner which strengthens the autogenic power of skin.

keep out of reach of the children

INDICATIONS AND USAGE

apply proper amount to the skin

WARNINGS

For external use only
When using this product

■ if the following symptoms occurs after use, stop use and consult with a skin specialist

red specks, swelling, itching

■ don’t use on the part where there is injury, eczema, or dermatitis

Keep out of reach of children

■ if swallowed, get medical help or contact a person control center immediately